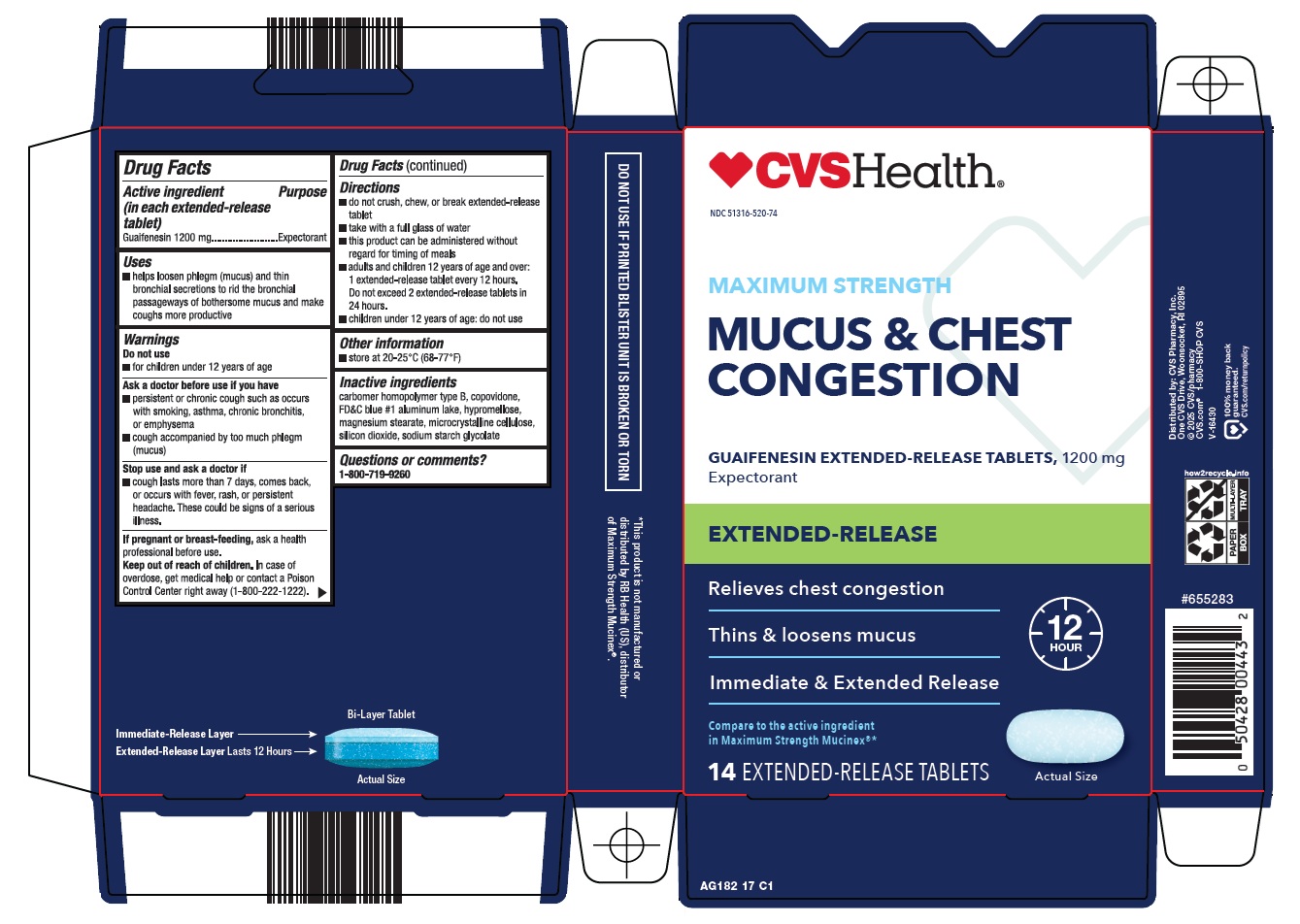 DRUG LABEL: MUCUS AND CHEST CONGESTION
NDC: 51316-520 | Form: TABLET, MULTILAYER, EXTENDED RELEASE
Manufacturer: CVS WOONSOCKET PRESCRIPTION CENTER, INCORPORATED
Category: otc | Type: HUMAN OTC DRUG LABEL
Date: 20260217

ACTIVE INGREDIENTS: GUAIFENESIN 1200 mg/1 1
INACTIVE INGREDIENTS: CARBOMER HOMOPOLYMER TYPE B (ALLYL PENTAERYTHRITOL CROSSLINKED); COPOVIDONE K25-31; FD&C BLUE NO. 1 ALUMINUM LAKE; HYPROMELLOSE, UNSPECIFIED; MAGNESIUM STEARATE; MICROCRYSTALLINE CELLULOSE; SILICON DIOXIDE; SODIUM STARCH GLYCOLATE TYPE A

CVS Pharmacy, Inc. Mucus & Chest Congestion Drug Facts

Active ingredient (in each extended-release tablet)

Guaifenesin 1200 mg

Purpose

Expectorant

Uses

- helps loosen phlegm (mucus) and thin bronchial secretions to rid the bronchial passageways of bothersome mucus and make coughs more productive

Warnings

Ask a doctor before use if you have

- persistent or chronic cough such as occurs with smoking, asthma, chronic bronchitis, or emphysema
- cough accompanied by too much phlegm (mucus)

Stop use and ask a doctor if

- cough lasts more than 7 days, comes back, or occurs with fever, rash, or persistent headache.

These could be signs of a serious illness.

If pregnant or breast-feeding,

ask a health professional before use.

Keep out of reach of children.

In case of overdose, get medical help or contact a Poison Control Center right away (1-800-222-1222).

Directions

- do not crush, chew, or break extended-release tablet
- take with a full glass of water
- this product can be administered without regard for timing of meals
- adults and children 12 years of age and over: 1 extended-release tablet every 12 hours. Do not exceed 2 extended-release tablets in 24 hours.
- children under 12 years of age: do not use

Other information

- store at 20-25°C (68-77°F)

Inactive ingredients

carbomer homopolymer type B, copovidone, FD&C blue #1 aluminum lake, hypromellose, magnesium stearate, microcrystalline cellulose, silicon dioxide, sodium starch glycolate

Questions or comments?

1-800-719-9260

Package/Label Principal Display Panel

CVS Health®

MAXIMUM STRENGTH

MUCUS & CHEST CONGESTION

GUAIFENESIN EXTENDED-RELEASE TABLETS, 1200 mg

Expectorant

EXTENDED-RELEASE

Relieves chest congestion

Thins & loosens mucus

Immediate & Extended Release

12 HOUR

Compare to the active ingredient in Maximum Strength Mucinex®

14 EXTENDED-RELEASE TABLETS

Actual Size